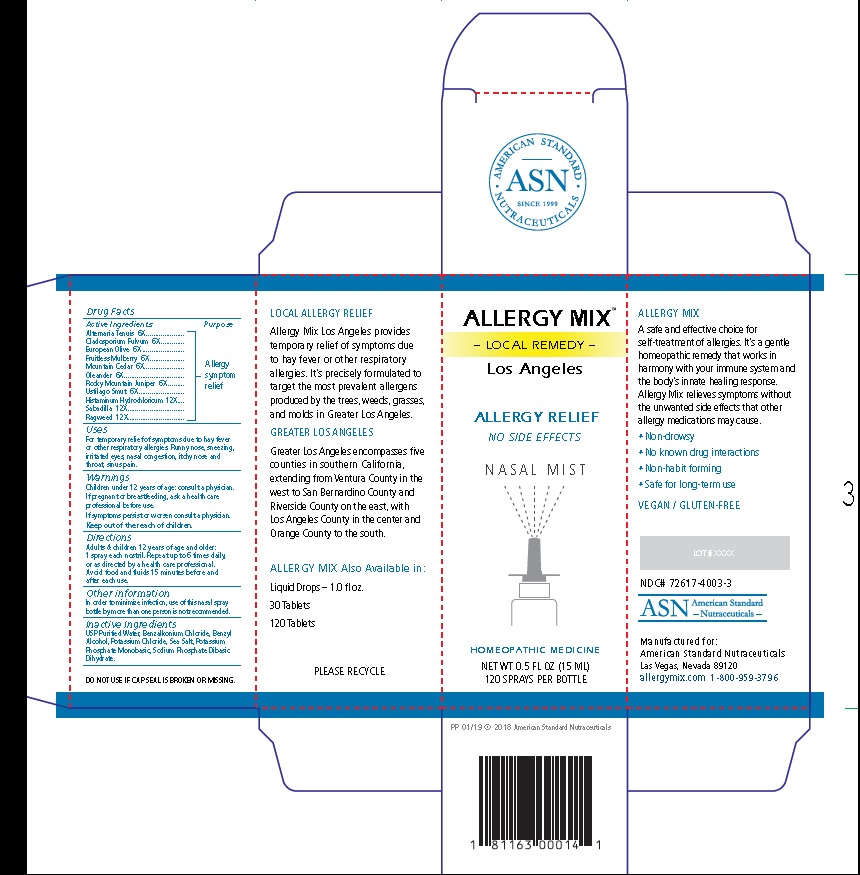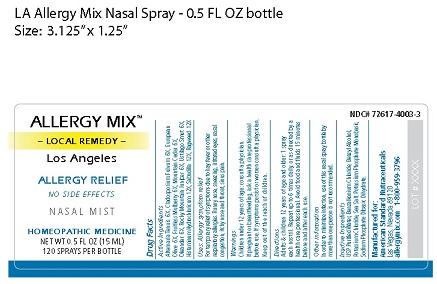 DRUG LABEL: ALLERGY MIX
NDC: 72617-4003 | Form: SPRAY
Manufacturer: ASN
Category: homeopathic | Type: HUMAN OTC DRUG LABEL
Date: 20190213

ACTIVE INGREDIENTS: ALTERNARIA ALTERNATA 6 [hp_X]/15 mL; PASSALORA FULVA 6 [hp_X]/15 mL; OLEA EUROPAEA FLOWER 6 [hp_X]/15 mL; WHITE MULBERRY 6 [hp_X]/15 mL; JUNIPERUS ASHEI POLLEN 6 [hp_X]/15 mL; NERIUM OLEANDER FLOWER 6 [hp_X]/15 mL; JUNIPERUS SCOPULORUM POLLEN 6 [hp_X]/15 mL; USTILAGO MAYDIS 6 [hp_X]/15 mL; HISTAMINE DIHYDROCHLORIDE 12 [hp_X]/15 mL; SCHOENOCAULON OFFICINALE SEED 12 [hp_X]/15 mL; AMBROSIA ARTEMISIIFOLIA 12 [hp_X]/15 mL
INACTIVE INGREDIENTS: WATER; BENZALKONIUM CHLORIDE; BENZYL ALCOHOL; POTASSIUM CHLORIDE; SEA SALT; POTASSIUM PHOSPHATE, MONOBASIC; SODIUM PHOSPHATE DIBASIC DIHYDRATE

ALLERGY MIX Los Angeles

Active Ingredients:
Alternaria Tenuis 6X
Cladosporium Fulvum 6X
European Olive 6X
Fruitless Mulberry 6X
Mountain Cedar 6X
Oleander 6X
Rocky Mountain Juniper 6X
Ustilago Smut 6X
Histaminum Hydrochloricum 12X
Sabadilla 12X
Ragweed 12X

Purpose: Allergy symptom relief

Uses
For temporary relief of symptoms due to hay fever
or other respiratory allergies. Runny nose, sneezing,
irritated eyes, nasal congestion, itchy nose and
throat, sinus pain.

Warnings
Children under 12 years of age: consult a physician.

If pregnant or breastfeeding, ask a health care
professional before use.
If symptoms persist or worsen consult a physician.

Keep out of the reach of children.

Directions
Adults & children 12 years of age and older: 1 spray
each nostril. Repeat up to 6 times daily, or as directed by a
health care professional. Avoid food and fluids 15 minutes
before and after each use.

Other information
In order to minimize infection, use of this nasal spray bottle by
more than one person is not recommended.

Inactive Ingredients
USP Purified Water, Benzalkonium Chloride, Benzyl
Alcohol, Potassium Chloride, Sea Salt, Potassium
Phosphate Monobasic, Sodium Phosphate Dibasic
Dihydrate.

Principal Display Package

AMERICAN STANDARD
• ASN •

SINCE 1999

NUTRACEUTICALS

ALLERGY MIX™
– LOCAL REMEDY –
Los Angeles

ALLERGY RELIEF
NO SIDE EFFECTS

N A S A L M I S T

HOMEOPATHIC MEDICINE

NET WT 0.5 FL OZ (15 ML)
120 SPRAYS PER BOTTLE

PP 01/19 © 2018 American Standard Nutraceuticals

1 81163 00014 1

LOCAL ALLERGY RELIEF

Allergy Mix Los Angeles provides
temporary relief of symptoms due
to hay fever or other respiratory
allergies. It’s precisely formulated to
target the most prevalent allergens
produced by the trees, weeds, grasses,
and molds in Greater Los Angeles.

GREATER LOS ANGELES

Greater Los Angeles encompasses five
counties in southern California,
extending from Ventura County in the
west to San Bernardino County and
Riverside County on the east, with
Los Angeles County in the center and
Orange County to the south.

ALLERGY MIX Also Available in:

Liquid Drops – 1.0 fl oz.

30 Tablets

120 Tablets

PLEASE RECYCLE

DO NOT USE IF CAP SEAL IS BROKEN OR MISSING.

ALLERGY MIX

A safe and effective choice for
self-treatment of allergies. It’s a gentle
homeopathic remedy that works in
harmony with your immune system and
the body’s innate healing response.
Allergy Mix relieves symptoms without
the unwanted side effects that other
allergy medications may cause.

• Non-drowsy

• No known drug interactions

• Non-habit forming

• Safe for long-term use

VEGAN / GLUTEN-FREE

LOT # XXXX

NDC# 72617-4003-3

ASN American Standard
- Nutraceuticals -

Manufactured for:
American Standard Nutraceuticals
Las Vegas, Nevada 89120
allergymix.com 1-800-959-3796

↓Bottle Label↓

res